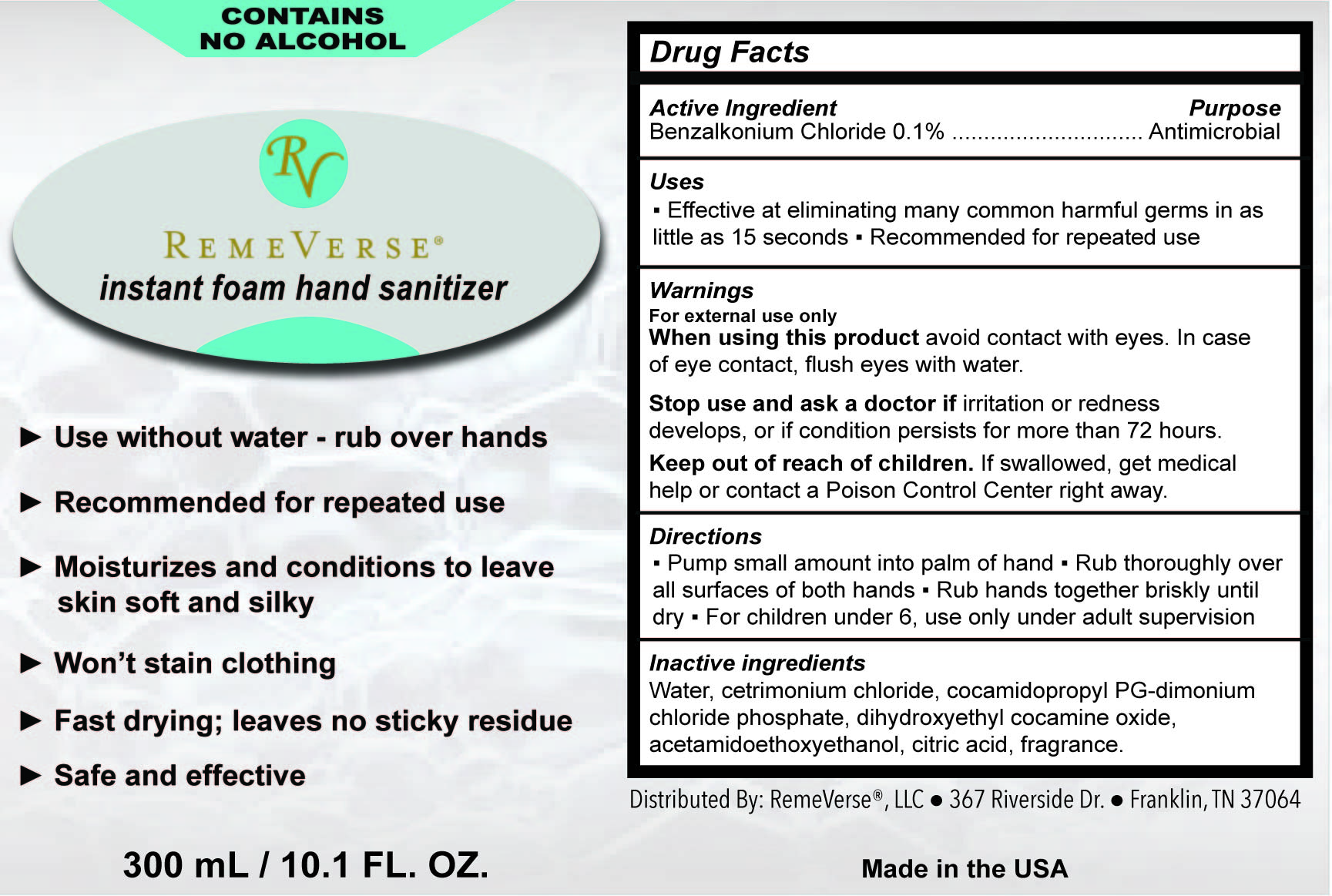 DRUG LABEL: RemeVerse Instant Foam Hand Sanitizer
NDC: 70317-145 | Form: LIQUID
Manufacturer: RemeVerse
Category: otc | Type: HUMAN OTC DRUG LABEL
Date: 20241216

ACTIVE INGREDIENTS: BENZALKONIUM CHLORIDE 0.1 g/300 mL
INACTIVE INGREDIENTS: DIHYDROXYETHYL COCAMINE OXIDE 0.1 g/300 mL; ANHYDROUS CITRIC ACID 0.1 g/300 mL; FRAGRANCE LAVENDER & CHIA F-153480 0.1 g/300 mL; CETRIMONIUM CHLORIDE 0.1 g/300 mL; COCAMIDOPROPYL PG-DIMONIUM CHLORIDE PHOSPHATE 0.1 g/300 mL

RemeVerse Instant Foam Hand Sanitizer

RemeVerse instant foam hand sanitizer

Water, cetrimonium chloride, cocamidopropyl PG-dimonium chloride phosphate, dihydroxyethyl cocamine oxide,
acetamidoethoxyethanol, citric acid, fragrance

RemeVerse Instant Foam Hand Sanitizer

Pump small amount into palm of hand ▪ Rub thoroughly over
all surfaces of both hands ▪ Rub hands together briskly until
dry ▪ For children under 6, use only under adult supervision

Topical Antimicrobial

Effective at eliminating many common harmful germs in as
little as 15 seconds ▪ Recommended for repeated use

Benzalkonium Chloride .1% Active

Benzalkonium Chloride - .1%

Warnings:

For external use only
When using this product avoid contact with eyes. In case
of eye contact, flush eyes with water.

Safety Warning

Stop use and ask a doctor if irritation or redness
develops, or if condition persists for more than 72 hours.

Warning - Children

Keep out of reach of children. If swallowed, get medical
help or contact a Poison Control Center right away.

Purpose - Antimicrobial

Antimicrobial

Label

Remeverse Hand Sanitizer Label 300ml lower resolution.jpg